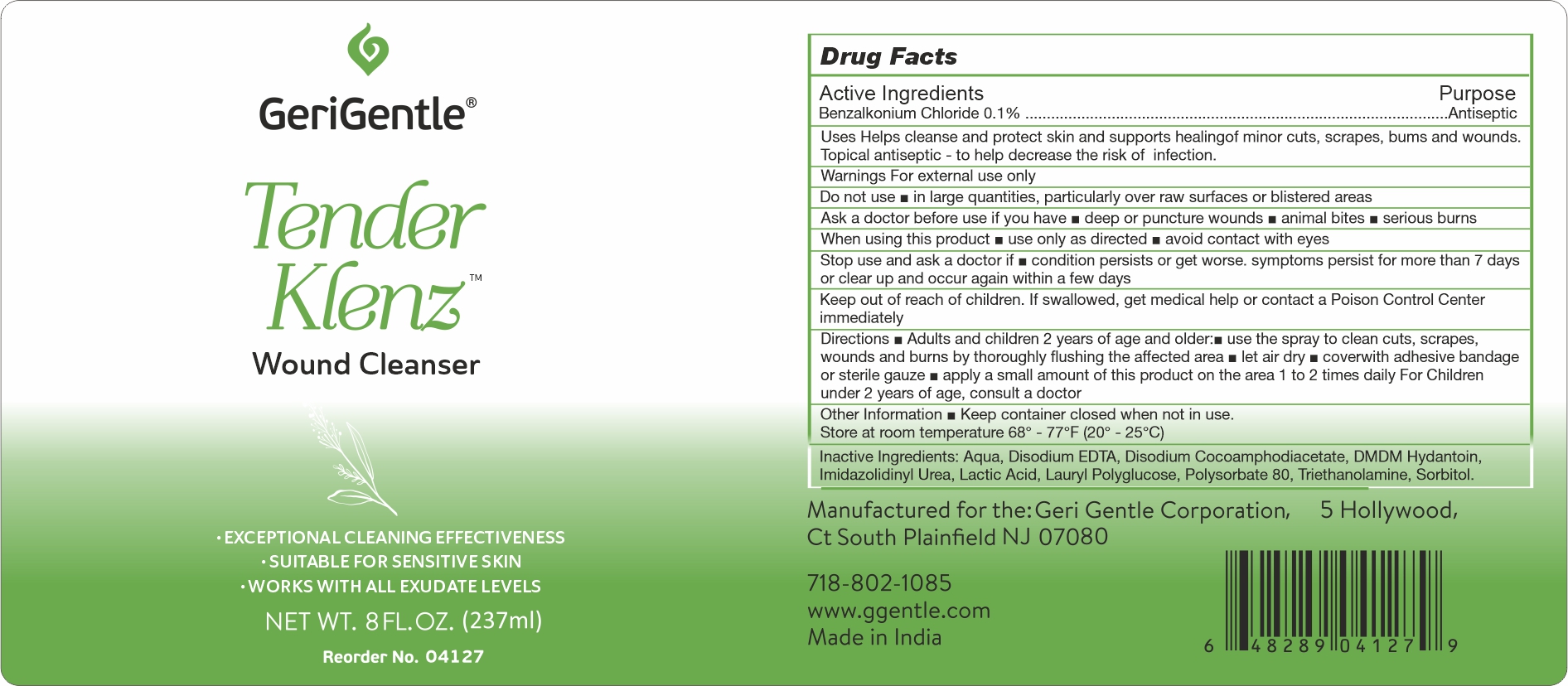 DRUG LABEL: BZK CLEANSER
NDC: 69771-062 | Form: SOLUTION
Manufacturer: Geri-Gentle Corporation
Category: otc | Type: HUMAN OTC DRUG LABEL
Date: 20251017

ACTIVE INGREDIENTS: BENZALKONIUM CHLORIDE 0.1 g/100 g
INACTIVE INGREDIENTS: EDETATE DISODIUM; LAURYL GLUCOSIDE; DMDM HYDANTOIN; POLYSORBATE 80; IMIDAZOLIDINYL UREA; LACTIC ACID, L-; TRIETHANOLAMINE; SORBITOL; DISODIUM COCOAMPHODIACETATE; WATER

GG TENDER KLENZ

Active Ingredient

Benzalkonium Chloride 0.1% w/w

Purpose

Antiseptic

Uses

- helps cleanse and protect skin and support healing of minor cuts, scrapes, burns and wounds.
- Topical antiseptic-to hel decrease the risk of infection.

For External Use Only

Do not use

- in large quantities, particularly over raw surfaces or blistered areas

Ask a doctor before use if you have

- deep or punctured wonds
- animal bites
- serious burns

When using this product

- use only as directed
- avoid contact with eyes

Stop use and ask a doctor if

- condition persists or get worse, symptoms persist for more than 7 days or clear up and occur again witin few days

Keep out of reach of children

if swallowed, get medical help or contact Poisn Control Center immediately

Directions

- Adults and children 2 years of age and older
- use the spray to clean cuts, scrapes, wounds and burns by thoroghly flushing the affected area
- let dry
- cover with adhesive bandage or sterile gauze
- apply a small amount of this product on the area 1or 2 times daily
- for children under 2 years of age,consult a doctor

other information

- Keep container close when not in use
- Store at room temprature 68 -77 F (20-25 C)

Inactive Ingredients

Water, Disodium EDTA, Disodium Cocoamphodiacetate, DMDM Hydantoin, Imidazolidinyl Urea, Lactic Acid, Lauryl Polyglucose, Polysorbate 80, Triethanolamine, Sorbitol